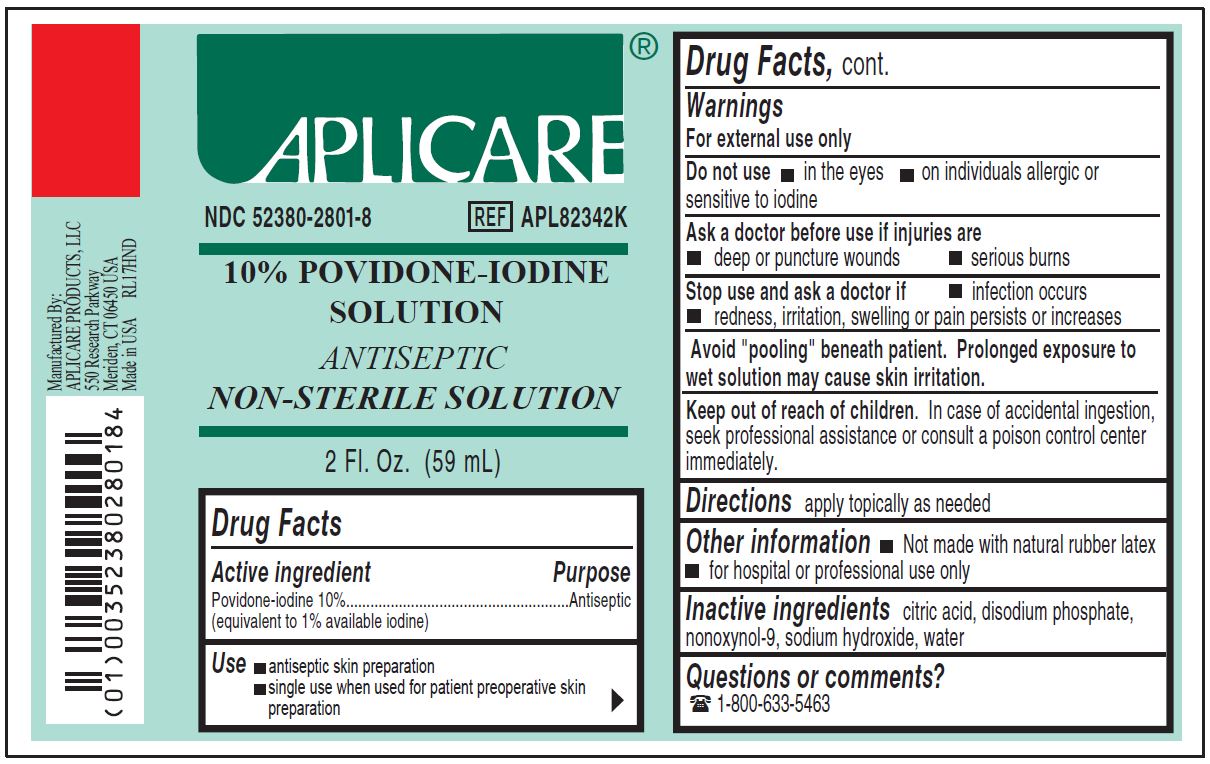 DRUG LABEL: Aplicare Povidone-Iodine
NDC: 52380-2801 | Form: SOLUTION
Manufacturer: Aplicare Products, LLC
Category: otc | Type: HUMAN OTC DRUG LABEL
Date: 20251218

ACTIVE INGREDIENTS: POVIDONE-IODINE 10 mg/1 mL
INACTIVE INGREDIENTS: CITRIC ACID MONOHYDRATE; SODIUM PHOSPHATE, DIBASIC; SODIUM HYDROXIDE; NONOXYNOL-9; WATER

2801Aplicare Povidone Iodine Solution

Active ingredient

Povidone-iodine 10%
(equivalent to 1% available iodine)

Purpose

Antiseptic

Use

- • antiseptic skin preparation
- • single use when used for patient preoperative skin preparation

Warnings

- For external use only
- Avoid "pooling" beneath patient. Prolonged exposure to wet solution may cause skin irritation.

Do not use

- • in the eyes
- • on individuals allergic or sensitive to iodine

Ask a doctor before use if injuries are

- • deep or puncture wounds
- • serious burns

Stop use and ask a doctor if

- • infection occurs
- • redness, irritation, swelling or pain persists or increases

Keep out of reach of children.

In case of accidental ingestion, seek professional assistance or consult a poison control center immediately.

Directions

- apply locally as needed

Other information

- • not made with natural rubber latex
- • for hospital or professional use only

Inactive ingredients

citric acid, disodium phosphate, nonoxynol-9, sodium hydroxide, water

Manufacturing Information

Manufactured by:

Aplicare Products, LLC

550 Research Way, Meriden, CT 06450 USA

Made in USA

REF: APL82342K

RL17HND